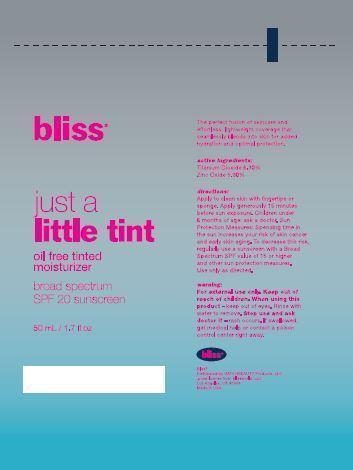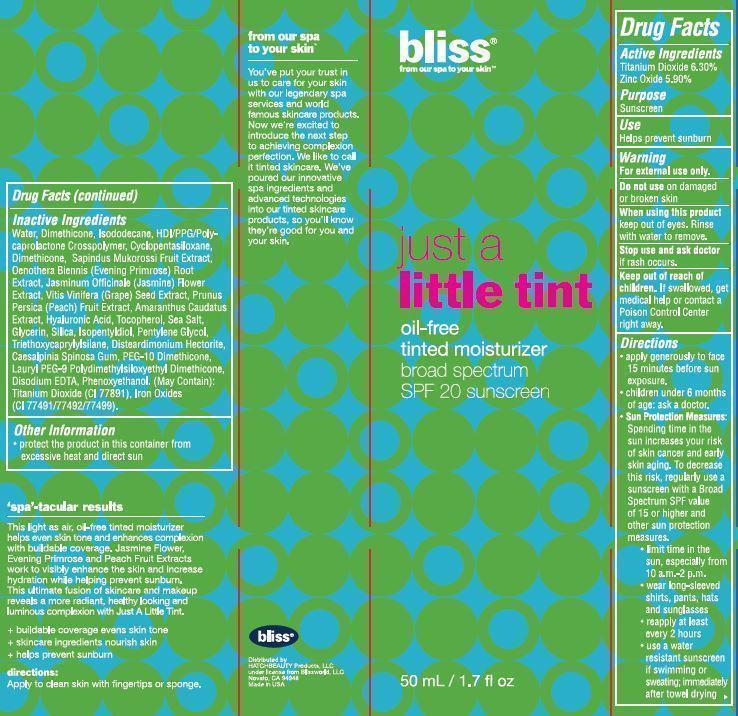 DRUG LABEL: TINTED MOISTURIZER
NDC: 69863-102 | Form: LOTION
Manufacturer: HATCHBEAUTY PRODUCTS LLC
Category: otc | Type: HUMAN OTC DRUG LABEL
Date: 20150625

ACTIVE INGREDIENTS: TITANIUM DIOXIDE 6.30 g/100 mL; ZINC OXIDE 5.90 g/100 mL
INACTIVE INGREDIENTS: WATER; DIMETHICONE; ISODODECANE; HEXAMETHYLENE DIISOCYANATE; CYCLOMETHICONE 5; SAPINDUS MUKOROSSI FRUIT; OENOTHERA BIENNIS ROOT; JASMINUM OFFICINALE FLOWER; VITIS VINIFERA SEED; PEACH; AMARANTHUS CAUDATUS WHOLE; HYALURONIC ACID; TOCOPHEROL; SEA SALT; GLYCERIN; SILICON DIOXIDE; ISOPENTYLDIOL; PENTYLENE GLYCOL; TRIETHOXYCAPRYLYLSILANE; DISTEARDIMONIUM HECTORITE; CAESALPINIA SPINOSA RESIN; PEG-10 DIMETHICONE (600 CST); LAURYL PEG-9 POLYDIMETHYLSILOXYETHYL DIMETHICONE; EDETATE DISODIUM; PHENOXYETHANOL; FERRIC OXIDE RED; FERRIC OXIDE YELLOW; FERROSOFERRIC OXIDE

ACTIVE INGREDIENTS

Titanium Dioxide 6.30%

Zinc Oxide 5.90%

PURPOSE

Sunscreen

USE

Helps prevent sunburn

WARNINGS

Warning
• For external use only.
• Do not use on damaged or broken skin

WHEN USING THIS PRODUCT

• Keep out of eyes. Rinse with water to remove.

STOP USE AND ASK DOCTOR

• If rash occurs.

• Keep out of reach of children. If product is swallowed, get medical help or contact a Poison Control Center right away.

DIRECTIONS

• Apply generously to face 15 minutes before sun exposure.

• Children under 6 months of age: ask a doctor.

Sun Protection Measures:

Spending time in the sun increases your risk of skin cancer and early skin aging. To decrease this risk, regularly use a sunscreen with a Broad Spectrum SPF value of 15 or higher and other sun protection measures.

• limit time in the sun, especially from 10 a.m.-2 p.m.

• wear long-sleeved shirts, pants, hats and sunglasses

• reapply at least every 2 hours

• use a water resistant sunscreen if swimming or sweating; immediately after towel drying

INACTIVE INGREDIENTS

Water, Dimethicone, Isododecane, HDI/PPG/Polycaprolactone Crosspolymer, Cyclopentasiloxane, Sapindus Mukorossi Fruit Extract, Oenothera Biennis (Evening Primrose) Root Extract, Jasminum Officinale (Jasmine) Flower Extract, Vitis Vinifera (Grape) Seed Extract, Prunus Persica (Peach) Fruit Extract, Amaranthus Caudatus Extract, Hyaluronic Acid, Tocopherol, Sea Salt, Glycerin, Silica, Isopentyldiol, Pentylene Glycol, Triethoxycaprylylsilane, Disteardimonium Hectorite, Caesalpinia Spinosa Gum, PEG-10 Dimethicone, Lauryl PEG-9 Polydimethylsiloxyethyl Dimethicone, Disodium EDTA, Phenoxyethanol. (May Contain): Titanium Dioxide (CI 77891), Iron Oxides (CI 77491/77492/77499).

OTHER INFORMATION

• protect the product in this container from excessive heat and direct sun